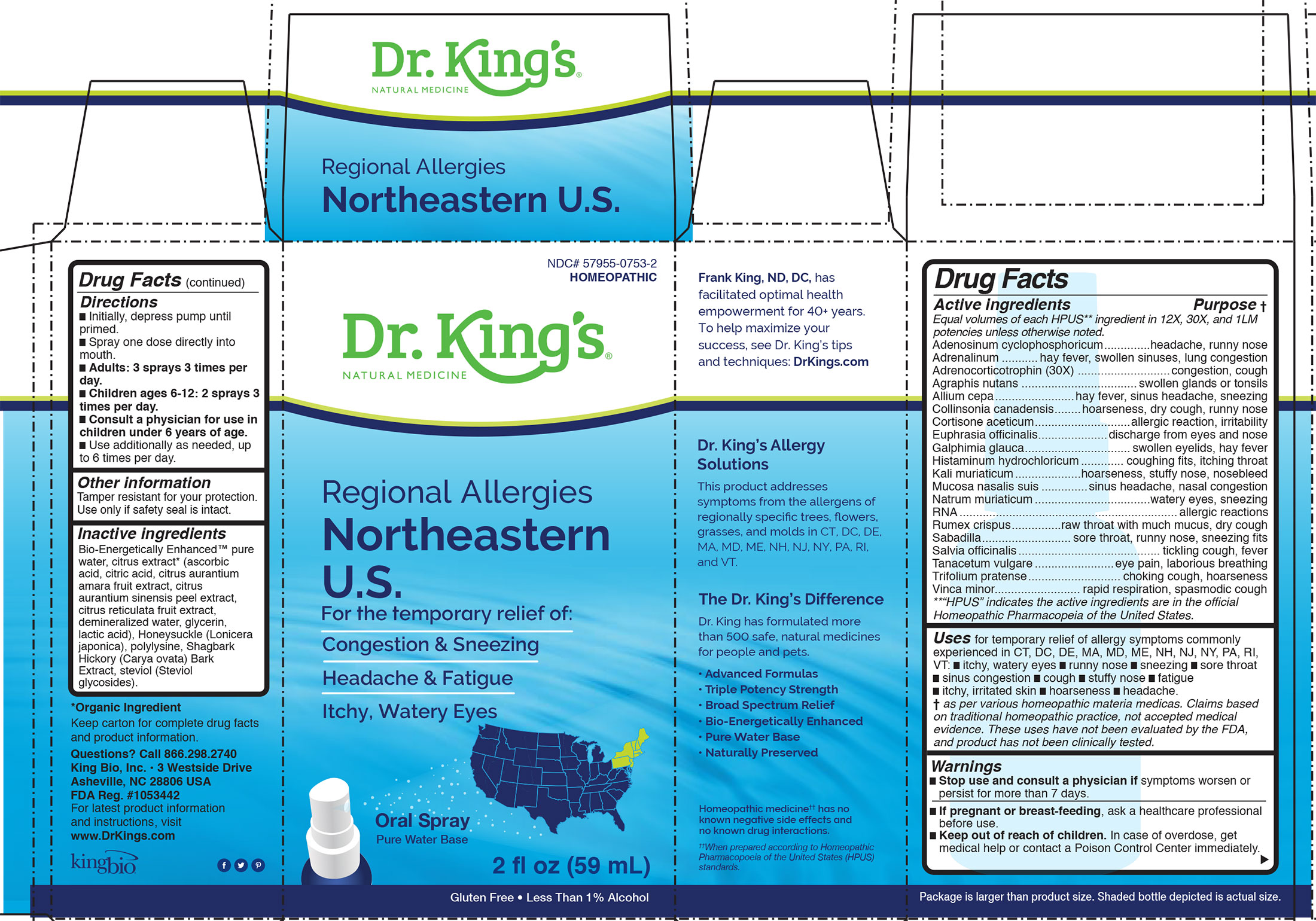 DRUG LABEL: Regional Allergies Northeastern US
NDC: 57955-0753 | Form: LIQUID
Manufacturer: King Bio Inc,
Category: homeopathic | Type: HUMAN OTC DRUG LABEL
Date: 20200708

ACTIVE INGREDIENTS: ADENOSINE CYCLIC PHOSPHATE 12 [hp_X]/59 mL; EPINEPHRINE 12 [hp_X]/59 mL; CORTICOTROPIN 12 [hp_X]/59 mL; HYACINTHOIDES NON-SCRIPTA 12 [hp_X]/59 mL; ONION 12 [hp_X]/59 mL; COLLINSONIA CANADENSIS ROOT 12 [hp_X]/59 mL; CORTISONE ACETATE 12 [hp_X]/59 mL; EUPHRASIA STRICTA 12 [hp_X]/59 mL; GALPHIMIA GLAUCA FLOWERING TOP 12 [hp_X]/59 mL; HISTAMINE DIHYDROCHLORIDE 12 [hp_X]/59 mL; POTASSIUM CHLORIDE 12 [hp_X]/59 mL; SUS SCROFA NASAL MUCOSA 12 [hp_X]/59 mL; SODIUM CHLORIDE 12 [hp_X]/59 mL; SACCHAROMYCES CEREVISIAE RNA 12 [hp_X]/59 mL; RUMEX CRISPUS ROOT 12 [hp_X]/59 mL; SCHOENOCAULON OFFICINALE SEED 12 [hp_X]/59 mL; SAGE 12 [hp_X]/59 mL; TANACETUM VULGARE TOP 12 [hp_X]/59 mL; TRIFOLIUM PRATENSE FLOWER 12 [hp_X]/59 mL; VINCA MINOR 12 [hp_X]/59 mL
INACTIVE INGREDIENTS: WATER; CARYA OVATA BARK; CITRUS BIOFLAVONOIDS; LONICERA JAPONICA FLOWER; POLYEPSILON-LYSINE (4000 MW); REBAUDIOSIDE A

Regional Allergies Northeastern U.S.

HPUS active ingredients

Equal volumes of each ingredient in 12X, 30X, and 1LM potencies.

Adenosinum cyclophosphoricum, Adrenalinum, Adrenocorticotrophin, Agraphis nutans, Allium cepa, Collinsonia canadensis, Cortisone aceticum, Euphrasia officinalis, Galphimia glauca, Histaminum hydrochloricum, Kali muriaticum, Mucosa nasalis suis, Natrum muriaticum, RNA, Rumex crispus, Sabadilla, Salvia officinalis, Tanacetum vulgare, Trifolium pratense, Vinca minor.

INDICATIONS AND USAGE

Uses for temporary relief of allergy symptoms commonly experienced in CT. DC. DE. MA. ME, MD. NH. NJ. NY. PA. RI. VT.

- itchy, watery eyes
- runny nose
- sneezing
- sore throat
- sinus congestion
- cough
- stuffy nose
- fatigue
- itchy, irritated skin
- hoarseness
- headache

Warnings

Stop use and consult a physician if symptoms worsen or
persist for more than 7 days.

PREGNANCY OR BREAST FEEDING

If pregnant or breast-feeding, ask a healthcare professional
before use.

Keep out of reach of children. In case of overdose, get
medical help or contact a Poison Control Center immediately.

Directions

- Initially, depress pump until primed.
- Spray one dose directly into mouth
- Adults: 3 sprays 3 times per day.
- Children ages 6-12: 2 sprays 3 times per day.
- Consult a physician for use in children under 6 years of age.
- Use additionally as needed, up to 6 times per day.

STORAGE AND HANDLING

Tamper resistant for your protection. Use only if safety seal is intact.

Inactive ingredients
Bio-Energetically Enhanced™ pure
water, citrus extract* (ascorbic
acid, citric acid, citrus aurantium
amara fruit extract, citrus
aurantium sinensis peel extract,
citrus reticulata fruit extract,
demineralized water, glycerin,
lactic acid), Honeysuckle (Lonicera
japonica), polylysine, Shagbark
Hickory (Carya ovata) Bark
Extract, steviol (Steviol
glycosides).

PURPOSE

Drug Facts__________________________________________________________________________________________________________

HPUS active ingredients Purpose

Equal volumes ofeach ingredient in 12X, 30X, and LM1 potencies.

Adenosinum cyclophosphoricum.............................................headache, runny nose

Adrenalinum........................................................................hay fever, swollen sinuses, lung congestion

Adrenocorticotrophin (30X)....................................................congestion, cough

Agraphis nutans....................................................................swollen glands or tonsils

Allium cepa...........................................................................hay fever, sinus headache, sneezing

Collinsonia canadensis............................................................hoarseness, dry cough, runny nose

Cortisone aceticum................................................................allergic reaction, irritability

Euphrasia officinalis...............................................................discharge from eyes and nose

Galphimia glauca...................................................................swollen eyelids, hay fever

Histaminum hydrochloricum....................................................coughing fits, itching throat

Kali muriaticum.....................................................................hoarseness, stuffy nose, nosebleed

Mucosa nasalis suis................................................................sinus headache, nasal congestion

Natrum muriaticum................................................................watery eyes, sneezing

RNA.....................................................................................allergic reactions

Rumex crispus.......................................................................raw throat with much mucus, dry cough

Sabadilla...............................................................................sore throat, runny nose, sneezing fits

Salvia officinalis.....................................................................tickling cough, fever

Tanacetum vulgare.................................................................eye pain, laborious breathing

Trifolium pratense..................................................................choking cough, hoarseness

Vinca minor...........................................................................rapid respiration, spasmodic cough

QUESTIONS

Keep carton for complete drug facts
and product information.

Questions? Call 866.298.2740
King Bio, Inc. • 3 Westside Drive
Asheville, NC 28806 USA
FDA Reg. #1053442

For latest product information
and instructions, visit
www.DrKings.com